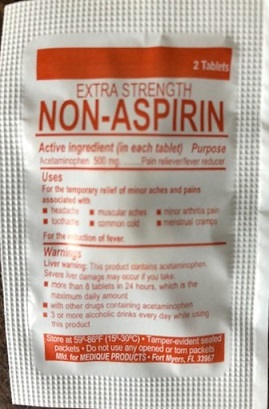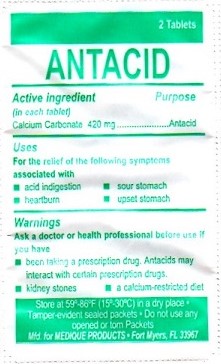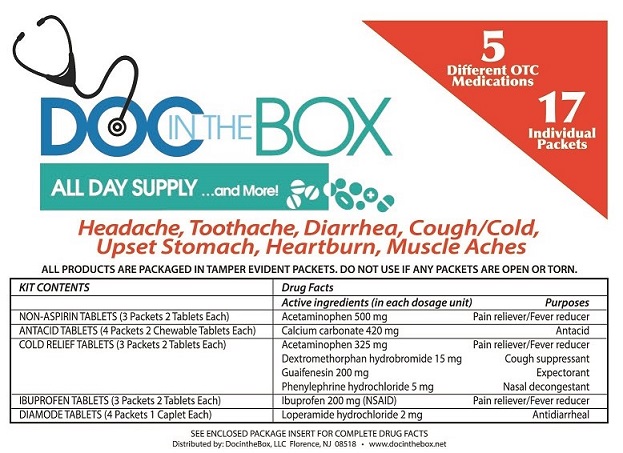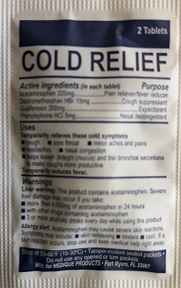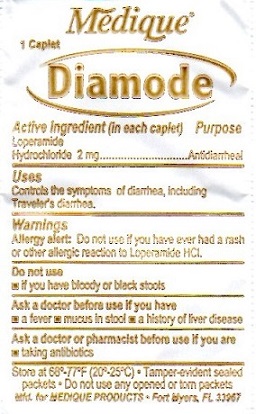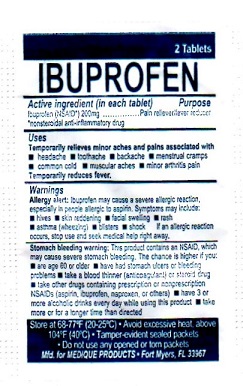 DRUG LABEL: Doc in the Box
NDC: 72082-001 | Form: KIT | Route: ORAL
Manufacturer: Doc in the Box LLC
Category: otc | Type: HUMAN OTC DRUG LABEL
Date: 20190101

ACTIVE INGREDIENTS: ACETAMINOPHEN 500 mg/1 1; CALCIUM CARBONATE 420 mg/1 1; ACETAMINOPHEN 325 mg/1 1; PHENYLEPHRINE HYDROCHLORIDE 5 mg/1 1; DEXTROMETHORPHAN HYDROBROMIDE 15 mg/1 1; GUAIFENESIN 200 mg/1 1; IBUPROFEN 200 mg/1 1; LOPERAMIDE HYDROCHLORIDE 2 mg/1 1
INACTIVE INGREDIENTS: SODIUM STARCH GLYCOLATE TYPE A POTATO; TITANIUM DIOXIDE; HYPROMELLOSES; MALTODEXTRIN; CELLULOSE, MICROCRYSTALLINE; POLYETHYLENE GLYCOL, UNSPECIFIED; STARCH, CORN; POVIDONE; STEARIC ACID; SUCROSE; ASPARTAME; CROSCARMELLOSE SODIUM; ACACIA; MAGNESIUM STEARATE; SORBITOL; MINERAL OIL; MALTODEXTRIN; CELLULOSE, MICROCRYSTALLINE; POVIDONE; SODIUM STARCH GLYCOLATE TYPE A CORN; STARCH, CORN; STEARIC ACID; TITANIUM DIOXIDE; POVIDONE K30; SILICON DIOXIDE; CARNAUBA WAX; STARCH, CORN; HYPROMELLOSE, UNSPECIFIED; FERRIC OXIDE RED; LACTOSE MONOHYDRATE; MAGNESIUM STEARATE; CELLULOSE, MICROCRYSTALLINE; POLYDEXTROSE; POLYETHYLENE GLYCOL, UNSPECIFIED; POLYVINYL ALCOHOL, UNSPECIFIED; SODIUM STARCH GLYCOLATE TYPE A POTATO; STEARIC ACID; TALC; STARCH, CORN; D&C YELLOW NO. 10; FD&C BLUE NO. 1; MAGNESIUM STEARATE; ANHYDROUS LACTOSE; CROSPOVIDONE; CORN OIL; POWDERED CELLULOSE; CROSCARMELLOSE SODIUM

DOC IN THE BOX ALL DAY SUPPLY

EXTRA STRENGTH NON-ASPIRIN

Purpose

Pain reliever/fever reducer

EXTRA STRENGTH NON-ASPIRIN

Active ingredient (in each tablet)

Acetaminophen 500 mg

EXTRA STRENGTH NON-ASPIRIN

Uses

For the temporary relief of minor aches and pains associated with

- headache
- muscular aches
- minor arthritis pain
- common cold
- toothache
- menstrual cramps

For the reduction of fever.

EXTRA STRENGTH NON-ASPIRIN

Warnings
Liver warning: This product contains acetaminophen. Severe liver damage may occur if you take:

- more than 8 tablets in 24 hours, which is the maximum daily amount
- with other drugs containing acetaminophen
- 3 or more alcoholic drinks every day while using this product

Allergy alert: acetaminophen may cause severe skin reactions. Symptoms may include:

- skin reddening
- blisters
- rash

If a skin reaction occurs, stop use and seek medical help right away.

EXTRA STRENGTH NON-ASPIRIN

Do not use

- with any other drug containing acetaminophen (prescription or nonprescription). If you are not sure whether a drug contains acetaminophen, ask a doctor or pharmacist.
- for more than 10 days for pain unless directed by a doctor
- for more than 3 days for fever unless directed by a doctor

EXTRA STRENGTH NON-ASPIRIN

Ask a doctor before use if you have liver disease

EXTRA STRENGTH NON-ASPIRIN

Ask a doctor or pharmacist before use if you are taking the blood thinning drug warfarin

EXTRA STRENGTH NON-ASPIRIN

Stop using and ask a doctor if

- symptoms do not improve
- new symptoms occur
- pain or fever persists or gets worse
- redness or swelling is present

EXTRA STRENGTH NON-ASPIRIN

If pregnant or breast-feeding, ask a health professional before use.

EXTRA STRENGTH NON-ASPIRIN

Keep out of reach of children. In case of overdose, get medical help or contact a Poison Control Center right away. Prompt medical attention is critical for adults as well as for children even if you do not notice any signs or symptoms.

EXTRA STRENGH NON-ASPIRIN

Directions

- do not use more than directed

Adults and children:; (12 years and older) | Take 2 tablets with water every 4 to 6 hours as needed.; Do not take more than 8 tablets in 24 hours.
Children under 12 years: | Do not give this adult strength product to children under; 12 years of age; this will provide more than the recommended; dose (overdose) and may cause liver damage.

EXTRA STRENGTH NON-ASPIRIN

Other information

- store at room temperature 59° - 86°F (15° - 30°C)
- tamper evident sealed packets
- do not use any opened or torn packets

EXTRA STRENGTH NON-ASPIRIN

Inactive ingredients

corn starch, hypromellose, maltodextrin*, microcrystalline cellulose*, polyethylene glycol, povidone*, pregelatinized starch*, sodium starch glycolate*, stearic acid, titanium dioxide*.
* may contain

EXTRA STRENGTH NON-ASPIRIN

Questions? 1-800-634-7680

ANTACID

Active ingredient (in each tablet)

Calcium Carbonate 420 mg

ANTACID

Purpose

Antacid

ANTACID

Uses

For the relief of the following symptoms associated with

- acid indigestion
- sour stomach
- heartburn
- upset stomach

ANTACID

Warnings

ANTACID

Ask a doctor or health professional before use if you have

- been taking a prescription drug. Antacids may interact with certain prescription drugs
- kidney stones
- a calcium-restricted diet

ANTACID

Stop using this product and ask a doctor if symptoms last more than 2 weeks

ANTACID

Do not exceed recommended dosage.

If pregnant or breast-feeding, ask a health professional before use.

ANTACID

Keep out of the reach of children.

ANTACID

Directions

- do not use more than directed
- Adults and children (12 years and older): Chew 2 tablets every 2 or 3 hours as symptoms occur or as directed by a physician. Do not take more than 19 tablets in a 24 hour period, or use the maximum dosage of this product for more than 2 weeks, except under the advice and supervision of a physician.
- Children under 12 years: Do not give to children under 12 years of age.

ANTACID

Other information

- Phenylketonurics: contains phenylalanine 1.5 mg per tablet
- each tablet contains 168 mg of elemental calcium
- store at room temperature 59° - 86°F (15° - 30°C)
- tamper-evident sealed packets
- do not use any opened or torn packets

ANTACID

Inactive ingredients

aspartame*, croscarmellose sodium*, gum acacia*, magnesium stearate, maltodextrin, mineral oil*, mint flavor, sorbitol*, sucrose*.
* may contain

ANTACID

Questions or comments? call 1-800-634-7680

COLD RELIEF

Active ingredient (in each tablet)

Acetaminophen 325 mg

Dextromethorphan Hydrobromide 15 mg

Guaifenesin 200 mg

Phenylephrine Hydrochloride 5 mg

COLD RELIEF

Purpose

Pain reliever/fever reducer

Cough suppressant

Expectorant

Nasal decongestant

COLD RELIEF

Uses

Temporarily relieves these cold symptoms

- cough
- sore throat
- minor aches and pains
- headache
- nasal congestion
- helps loosen phlegm (mucus) and thin bronchial secretions to make coughs more productive

Temporarily reduces fever.

COLD RELIEF

Warnings

Liver warning: This product contains acetaminophen. Severe liver damage may occur if you take:

- more than 4,000 mg of acetaminophen in 24 hours
- with other drugs containing acetaminophen
- 3 or more alcoholic drinks every day while using this product

Allergy alert: acetaminophen may cause severe skin reactions. Symptoms may include:

- skin reddening
- blisters
- rash

If a skin reaction occurs, stop use and seek medical help right away.

Sore throat warning: If sore throat is severe, persists for more than 2 days, is accompanied or followed by fever, headache, rash, nausea or vomiting, consult a doctor promptly.

COLD RELIEF

Do not use

- with any other drug containing acetaminophen (prescription or nonprescription). If you are not sure whether a drug contains acetaminophen, ask a doctor or pharmacist.
- if you have ever had an allergic reaction to this product or any of its ingredients
- if you are now taking a prescription monoamine oxidase inhibitor (MAOI) (certain drugs for depression, psychiatric or emotional conditions, or Parkinson’s disease), or for 2 weeks after stopping the MAOI drug. If you do not know if your prescription drug contains an MAOI, ask a doctor or pharmacist before taking this product.

COLD RELIEF

- liver disease
- heart disease
- high blood pressure
- thyroid disease
- diabetes
- trouble urinating due to an enlarged prostate gland
- cough that occurs with too much phlegm (mucus)
- persistent or chronic cough that lasts as occurs with smoking, asthma, chronic bronchitis or emphysema

COLD RELIEF

Ask a doctor or pharmacist before use if you are

- taking the blood thinning drug warfarin

COLD RELIEF

When using this product

- do not use more than directed

COLD RELIEF

Stop use and ask a doctor if

- new symptoms occur
- redness or swelling is present
- pain or nasal congestion gets worse or lasts for more than 7 days
- fever gets worse or lasts for more than 3 days
- you get nervous, dizzy or sleepless
- cough comes back or occurs with rash or headache that lasts.

These could be signs of a serious condition.

COLD RELIEF

If pregnant or breast-feeding, ask a health professional before use.

COLD RELIEF

Keep out of reach of children. In case of overdose, get medical help or contact a Poison Control Center right away. Prompt medical attention is critical for adults as well as for children even if you do not notice any signs or symptoms.

COLD RELIEF

Directions

Adults and children:; (12 years and older) | Take 2 tablets with water every 6-8 hours as needed. Do; not take more than 8 tablets in 24 hours.
Children under 12 years: | Do not give to children under 12 years of age.

COLD RELIEF

Other information

- store at room temperature 59° - 86°F (15° - 30°C)
- avoid excessive heat and humidity
- tamper evident sealed packets
- do not use any opened or torn packets

COLD RELIEF

Inactive ingredients maltodextrin, microcrystalline cellulose, povidone, sodium starch glycolate, starch, stearic acid

COLD RELIEF

Questions?

1-800-634-7680

IBUPROFEN

Active ingredient (in each tablet)

Ibuprofen 200 mg (NSAID)*

*non-steroidal anti-inflammatory drug

IBUPROFEN

Purpose

Pain reliever/fever reducer

IBUPROFEN

Uses

Temporarily relieves minor aches and pains associated with

- headache
- toothache
- backache
- menstrual cramps
- common cold
- muscular aches
- minor arthritis pain

Temporarily reduces fever.

IBUPROFEN

Warnings

Allergy alert: Ibuprofen may cause a severe allergic reaction, especially in people allergic to aspirin. Symptoms may include:

- hives
- skin reddening
- asthma (wheezing)
- facial swelling
- rash
- shock
- blisters

If an allergic reaction occurs, stop use and seek medical help right away.

Stomach bleeding warning: This product contains an NSAID, which may cause severe stomach bleeding. The chance is higher if you:

- are age 60 or older
- have had stomach ulcers or bleeding problems
- taking a blood thinning (anticoagulant) or steroid drug
- take other drugs containing prescription or nonprescription NSAIDs (aspirin, ibuprofen, naproxen, or others)
- have 3 or more alcoholic drinks every day while using this product
- take more or for a longer time than directed

IBUPROFEN

Do not use

- if you have ever had an allergic reaction to any other pain reliever/fever reducer
- right before or after heart surgery

IBUPROFEN

Ask a doctor before use if

- stomach bleeding warning applies to you
- you have a history of stomach problems such as heartburn
- you have high blood pressure, heart disease, liver cirrhosis, or kidney disease
- you are taking a diuretic
- you have problems or serious side effects from taking pain relievers or fever reducers
- you have asthma

IBUPROFEN

Ask a doctor or pharmacist before use if you are

- taking aspirin for heart attack or stroke, because ibuprofen may decrease this benefit of aspirin
- taking any other drug
- under a doctor’s care for any serious condition

IBUPROFEN

When using this product

- the risk of heart attack or stroke may increase if you use more than directed or longer than directed
- take with food or milk if stomach upset occurs

IBUPROFEN

Stop use and ask a doctor if

- you experience any of the following signs of stomach bleeding

▪ feel faint ▪ vomit blood ▪ have bloody or black stools
▪ have stomach pain that does not get better

- pain gets worse or lasts for more than 10 days
- fever gets worse or lasts for more than 3 days
- redness or swelling is present in the painful area
- any new or unexpected symptoms occur

IBUPROFEN

If pregnant or breast-feeding, ask a health professional before use. It is especially important not to use ibuprofen during the last 3 months of pregnancy unless specifically directed to do so by a doctor because it may cause problems in the unborn child or complications during delivery.

IBUPROFEN

Keep out of reach of children. In case of overdose, get medical help or contact a Poison Control Center right away.

IBUPROFEN

Directions

- do not use more than directed
- the smallest effective dose should be used
- do not take longer than 10 days, unless directed by a doctor (see Warnings)

Adults and children:; (12 years and older) | Take 1 tablet every 4 to 6 hours while symptoms persist. If pain for fever; does not respond to 1 tablet, 2 tablets may be used. Do not exceed 6 tablets; in 24 hours, unless directed by a doctor.
Children under 12 years: | Do not give to children under 12 years of age.

IBUPROFEN

Other information

- read all product information before using
- store at 68° - 77°F (20° - 25°C)
- avoid excessive heat 104°F (above 40°C)
- tamper evident sealed packets
- do not use any opened or torn packet

IBUPROFEN

Inactive ingredients

carnauba wax*, corn starch, hypromellose*, iron oxide red, lactose*, magnesium stearate*, microcrystalline cellulose*, polydextrose*, polyethylene glycol, polyvinyl alcohol*, povidone (K-30)*, silicon dioxide, sodium starch glycolate, stearic acid, talc*, titanium dioxide

* may contain

IBUPROFEN

Questions or comments?1-800-634-7680

DIAMODE

Active ingredient (in each caplet)

Loperamide Hydrochloride 2 mg

DIAMODE

Purpose

Antidiarrheal

DIAMODE

Uses

Controls the symptoms of diarrhea, including Traveler's diarrhea

DIAMODE

Warnings

Allergy alert: Do not use if you have ever had a rash or other allergic reaction to Loperamide HCl

DIAMODE

Do not use if you have bloody or black stool

DIAMODE

Ask a doctor before use if you have

- a fever
- mucus in stool
- a history of liver disease

DIAMODE

Ask a doctor or pharmacist before use if you are taking antibiotics

DIAMODE

When using this product

- tiredness, drowsiness or dizziness may occur
- be careful when driving or operating machinery

DIAMODE

Stop use and ask a doctor if

- symptoms get worse
- diarrhea lasts more than 2 days
- upi get abdominal swelling or bulging. These may be signs of a serious condition.

DIAMODE

If you are pregnant or breast-feeding, ask a health professional before use

DIAMODE

Keep out of reach of children. In case of overdose, get medical help or contact a Poison Control Center right away.

DIAMODE

Directions

- do not use more than directed
- drink plenty of clear fluids to help prevent dehydration caused by diarrhea

Adults and children:; (12 years and older) | Take 2 caplets after the first loose stool; followed by 1 caplet after each subsequent; loose stool but no more than 4 caplets in 24 hours.
Children under 12 years: | Do not give to children under 12 years of age.

DIAMODE

Other information

- store at room temperature 68° - 77°F (20° - 25°C)
- tamper-evident sealed packets
- do not use any opened or torn packet

DIAMODE

Inactive ingredients anhydrous lactose, croscarmellose sodium, crospovidone, D&C Yellow #10, FD&C Blue #1, hydrogenated vegetable oil, magnesium stearate, powdered cellulose, pregelatinized starch

DIAMODE

Questions or comments? 1-800-634-7680

EXTRA STRENGTH NON-ASPIRIN

EXTRA STRENGTH

NON-ASPIRIN

2 Tablets

Mfd. for MEDIQUE PRODUCTS • Fort Myers, FL 33967

ANTACID

2 Tablets

Mfd for MEDIQUE PRODUCTS, Fort Myers, FL 33967

COLD RELIEF

2 Tablets

Mfd for MEDIQUE PRODUCTS, Fort Myers, FL 33967

IBUPROFEN

2 Tablets

Mfd. for: MEDIQUE PRODUCTS • Fort Myers, FL 33967

DIAMODE

Medique

Diamode

1 Caplet

Mfd. for MEDIQUE PRODUCTS, Fort Myers, FL 33967

OUTER KIT CARTON

DOC IN THE BOX

ALL DAY SUPPLY...and More!

5 Different OTC Medications

17 Individual Packets

Headache, Toothache, Diarrhea, Cough/Cold, Upset Stomach, Heartburn, Muscle Aches

ALL PRODUCTS ARE PACKAGED IN TAMPER EVIDENT PACKETS. DO NOT USE IF ANY PACKETS ARE OPEN OR TORN.

KIT CONTENTS | Drug Facts
 | Active ingredients (in each dosage unit | Purposes
NON-ASPIRIN TABLETS (3 Packets, 2 Tablets Each) | Acetaminophen 500 mg | Pain reliever/Fever reducer
ANTACID TABLETS (4 Packets, 2 Chewable Tablets Each) | Calcium Carbonate 420 mg | Antacid
COLD RELIEF TABLETS (3 Packets 2 Tablets Each) | Acetaminophen 325 mg; Dextromethorphan hydrobromide 15 mg; Guaifenesin 200 mg; Phenylephrine hydrochloride 5 mg | Pain reliever/Fever reducer; Cough suppressant; Expectorant; Nasal decongestant
IBUPROFEN TABLETS (3 Packets 2 Tablets Each) | Ibuprofen 200 mg (NSAID) | Pain reliever/Fever reducer
DIAMODE TABLETS (4Packets 1 Caplet Each) | Loperamide hydrochloride 2 mg | Antidiarrheal

SEE ENCLOSED PACKAGE INSERT FOR COMPLETE DRUG FACTS

Distributed by: DocintheBox, LLC, Florence, NJ 08518 • www.docinthebox.com